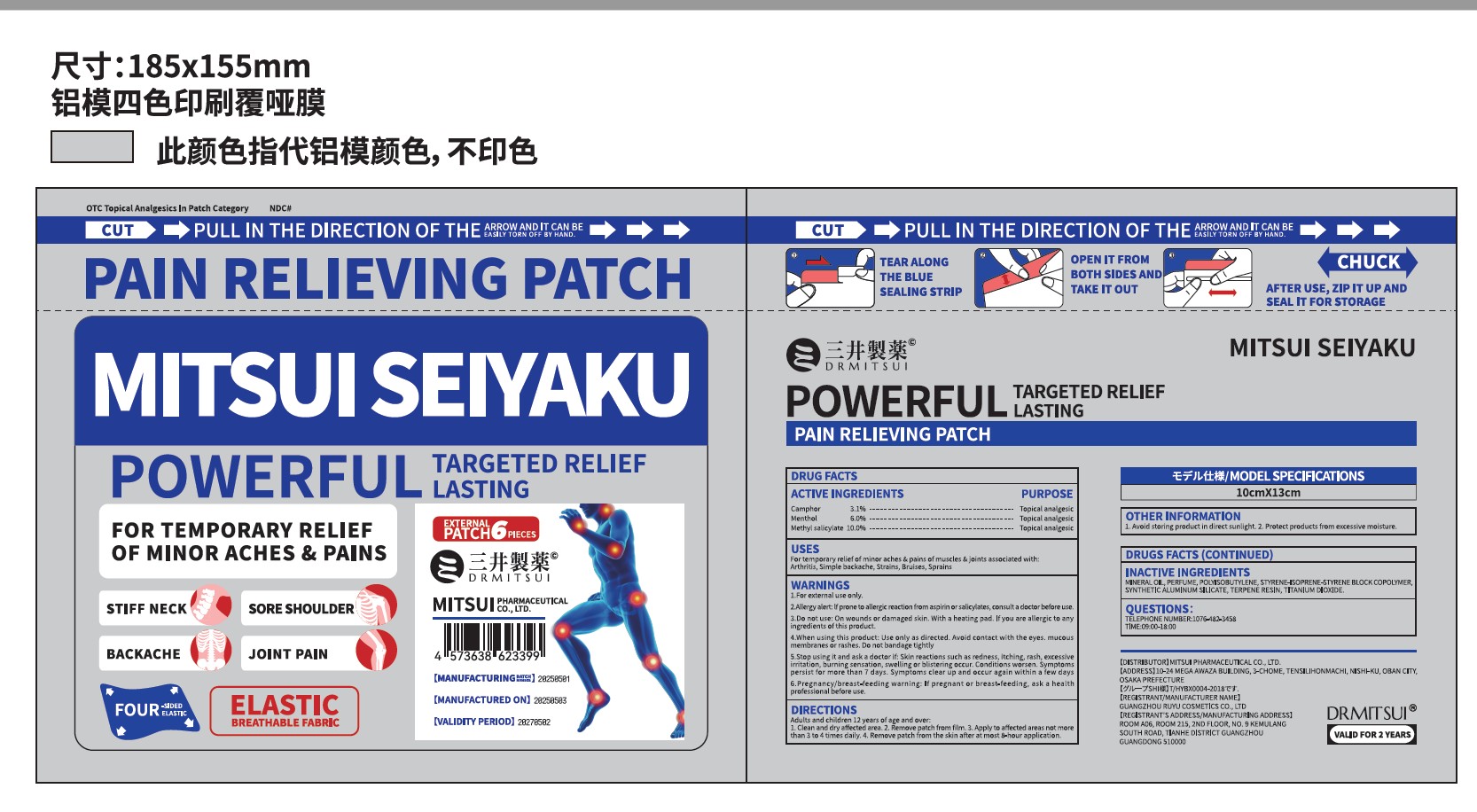 DRUG LABEL: DRMITSUI Pain Relieving Patch
NDC: 85713-101 | Form: PATCH
Manufacturer: Guangzhou Ruyu Cosmetics Co., Ltd
Category: otc | Type: HUMAN OTC DRUG LABEL
Date: 20251216

ACTIVE INGREDIENTS: MENTHOL 6 g/100 g; CAMPHOR, (-)- 3.1 g/100 g; METHYL SALICYLATE 10 g/100 g
INACTIVE INGREDIENTS: MINERAL OIL; POLYISOBUTYLENE 35-39; ALUMINUM SILICATE; TERPENE RESIN; STYRENE/ISOPRENE/STYRENE BLOCK COPOLYMER

ACTIVE INGREDIENT

ACTIVEINGREDIENTS
PURPOSE
CamphorMenthol
3.1%
Topical analgesicTopical analgesicTopical analgesic
6.0%
Methyl salicylate 10.0%

PURPOSE

For temporary relief of minor aches & pains of muscles & joints associated with:Arthritis, Simple backache, Strains, Bruises, Sprains

INACTIVE INGREDIENT

MINERAL OIL, PERFUME,POLYISOBUTYLENE, STYRENE-ISOPRENE-STYRENE BLOCK COPOLYMER.
SYNTHETIC ALUMINUM SILICATE,TERPENE RESIN, TITANIUM DIOXIDE.

WARNINGS

1.For external use only.
2.Allergy alert: lf prone to allergic reaction from aspirin or salicylates, consult a doctor before use3.Do not use: On wounds or damaged skin. With a heating pad. lf you are allergic to anyingredients of this product.
4.When using this product: Use only as directed. Avoid contact with the eyes. mucousmembranes or rashes. Do not bandage tightly
5.Stop using it and ask a doctor if: Skin reactions such as redness, itching, rash, excessiveirritation, burning sensation,swelling or blistering occur. Conditions worsen.Symptomspersist for more than 7 days. Symptoms clear up and occur again within a few days6.Pregnancy/breast-feeding warning: lf pregnant or breast-feeding, ask a healthprofessional before use.

DOSAGE AND ADMINISTRATION

Apply to affected areas not morethan 3 to 4 times daily.

Remove patch from the skin after at most 8-hour application.

DIRECTIONS
Adults and children 12 years of age and over:1. Clean and dry affected area. 2. Remove patch from film. 3. Apply to affected areas not morethan 3 to 4 times daily. 4. Remove patch from the skin after at most 8-hour application.

Keep out of children to reach